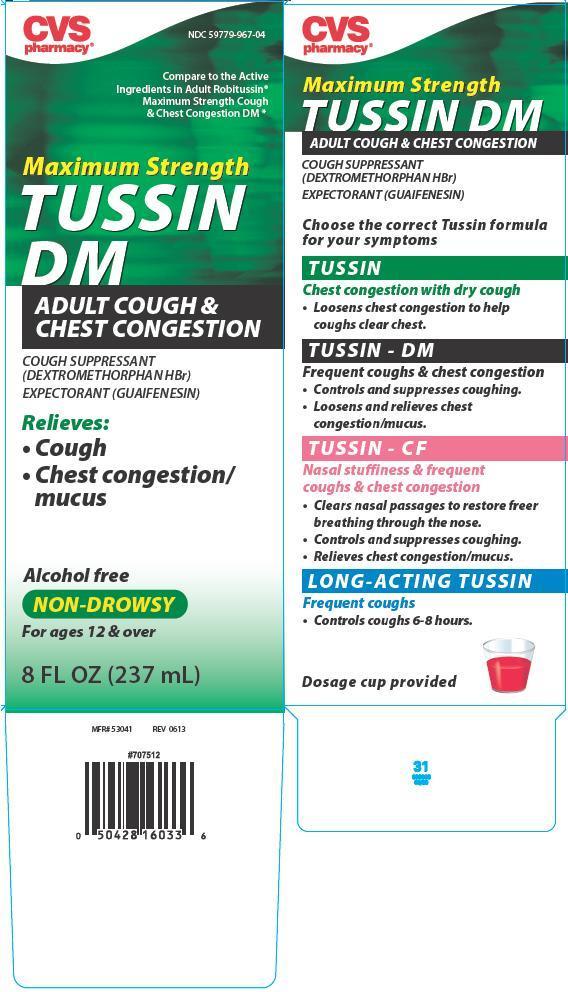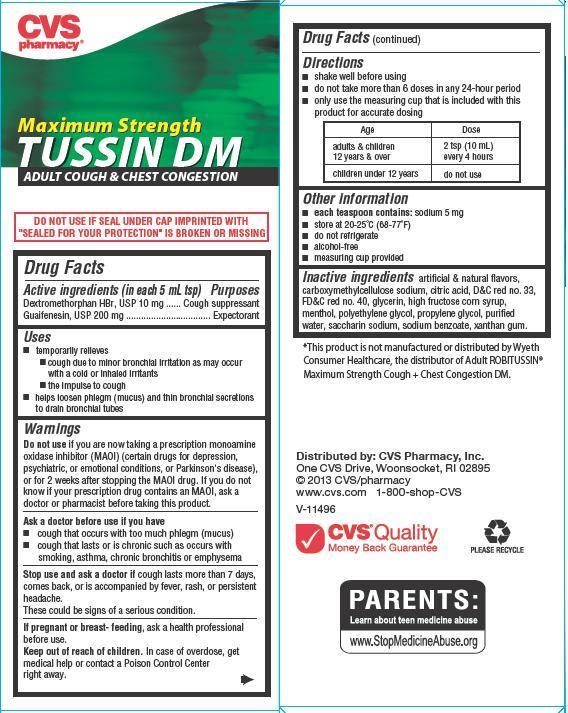 DRUG LABEL: Tussin DMMaximum Strength

                
NDC: 59779-967 | Form: LIQUID
Manufacturer: CVS Pharmacy
Category: otc | Type: HUMAN OTC DRUG LABEL
Date: 20130618

ACTIVE INGREDIENTS: DEXTROMETHORPHAN HYDROBROMIDE 10 mg/5 mL; GUAIFENESIN 200 mg/5 mL
INACTIVE INGREDIENTS: CARBOXYMETHYLCELLULOSE SODIUM; CITRIC ACID MONOHYDRATE; D&C RED NO. 33; FD&C RED NO. 40; GLYCERIN; HIGH FRUCTOSE CORN SYRUP; MENTHOL; POLYETHYLENE GLYCOL 400; PROPYLENE GLYCOL; WATER; SACCHARIN SODIUM; SODIUM BENZOATE; XANTHAN GUM

Maximum Strength Tussin DM

Active ingredients (in each 5 mL tsp)

Dextromethorphan HBr, USP 10mg

Guaifenesin, USP 200mg

Purposes

Cough suppressant

Expectorant

Uses

helps loosen phlegm (mucus) and thin bronchial secretions to drain bronchial tubes

temporarily relieves:

- cough due to minor bronchial irritation as may occur with a cold or inhaled irritants
- the impulse to cough

Warnings

Do not use if you are now taking a prescription monoamine oxidase inhibitor (MAOI) (certain drugs for depression, psychiatric, or emotional conditions or parkinson's disease), or for 2 weeks after stopping the MAOI drug. If you do not know if your prescription drug contains MAOI, ask a doctor or pharmacist before taking this product.

Ask a doctor before use if you have

- cough that occurs with too much phlegm (mucus)
- cough that lasts or is chronic such as occurs with smoking, asthma, chronic bronchitis or emphysema

Stop use and ask a doctor if

cough lasts more than 7 days, comes back, or is accompanied by fever, rash or persistent headache. These could be signs of a serious condition.

If pregnant or breast-feeding,

ask a health professional before use.

Keep out of reach of children. In case of overdose, get medical help or contact a Poison Control Center right away

Directions

- shake well before using
- do not take more than 6 doses in any 24-hour period
- only use the measuring cup that is included with this product for accurate dosing

Age | Dose
adults and children 12 years and over | 2 tsp (10ml) every 4 hours
children under 12 years | do not use

Other information

- each teaspoon contains: sodium 5 mg
- store at 20-25oC (68-77oF)
- do not refrigerate
- alcohol-free
- measuring cup provided

Inactive ingredients:

artificial and natural flavors, carboxymethylcellulose sodium, citric acid, Dand C red no. 33, FD and c red no. 40, glycerin, high fructose corn syrup, menthol, polyethylene glycol, propylene glycol, purified water, saccharin sodium, sodium benzoate, xanthan gum

Principal Display panel

NDC 59779-967-04
Compare to the active ingredients in Adult Robitussin Cough and Chest congestion
Maximum Strength
Tussin DM
Adult Cough and chest congestion
Cough Supressant (Dextromethorphan HBr)
Expectorant (Guaifenesin)
Relieves:
Cough
Chest congestion/mucus

alcohol free
Non-Drowsy
For ages 12 and over
8 fl oz (237 mL)
1 image
2 image